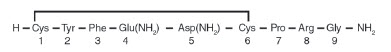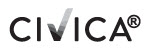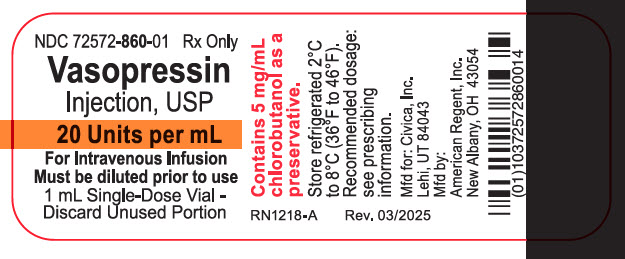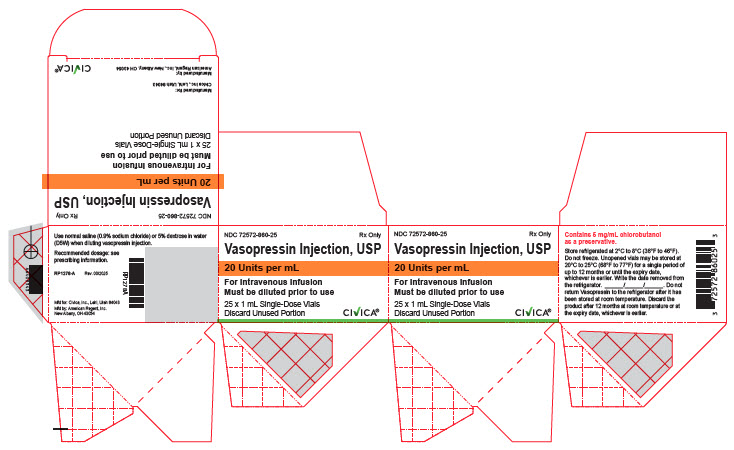 DRUG LABEL: Vasopressin
NDC: 72572-860 | Form: INJECTION, SOLUTION
Manufacturer: Civica, Inc.
Category: prescription | Type: HUMAN PRESCRIPTION DRUG LABEL
Date: 20250301

ACTIVE INGREDIENTS: VASOPRESSIN 20 [USP'U]/1 mL
INACTIVE INGREDIENTS: WATER; ACETIC ACID; SODIUM CHLORIDE 9 mg/1 mL; CHLOROBUTANOL 5 mg/1 mL

HIGHLIGHTS OF PRESCRIBING INFORMATION

These highlights do not include all the information needed to use VASOPRESSIN INJECTION safely and effectively. See full prescribing information for VASOPRESSIN INJECTION.
VASOPRESSIN injection, for intravenous use
Initial U.S. Approval: 2014

1 INDICATIONS AND USAGE

- Vasopressin injection is indicated to increase blood pressure in adults with vasodilatory shock who remain hypotensive despite fluids and catecholamines. (1)

2 DOSAGE AND ADMINISTRATION

- Dilute vasopressin injection with 0.9% Sodium Chloride Injection or 5% Dextrose Injection to either 0.1 units/mL or 1 unit/mL for intravenous administration. Discard unused diluted solution after 18 hours at room temperature or 24 hours under refrigeration. (2.1)
- Post-cardiotomy shock: 0.03 units/minute to 0.1 units/minute. (2.2)
- Septic shock: 0.01 units/minute to 0.07 units/minute. (2.2)

3 DOSAGE FORMS AND STRENGTHS

- Injection: 20 units/ mL in a single-dose vial and 200 units/10 mL (20 units/mL) in a multiple-dose vial. (3)

4 CONTRAINDICATIONS

- Vasopressin injection 1 mL single-dose vial and 10 mL multiple-dose vial are contraindicated in patients with known allergy or hypersensitivity to 8-L-arginine vasopressin or chlorobutanol. (4)

5 WARNINGS AND PRECAUTIONS

- Can worsen cardiac function. (5.1)
- Reversible diabetes insipidus (5.2)

6 ADVERSE REACTIONS

The most common adverse reactions include decreased cardiac output, bradycardia, tachyarrhythmias, hyponatremia and ischemia (coronary, mesenteric, skin, digital). (6)

To report SUSPECTED ADVERSE REACTIONS, contact American Regent, Inc. at 1-800-734-9236 or FDA at 1-800-FDA-1088 or www.fda.gov/medwatch.

7 DRUG INTERACTIONS

- Pressor effects of catecholamines and vasopressin injection are expected to be additive. (7.1)
- Indomethacin may prolong effects of vasopressin injection. (7.2)
- Co-administration of ganglionic blockers or drugs causing SIADH (syndrome of inappropriate antidiuretic hormone secretion) may increase the pressor response. (7.3, 7.4)
- Co-administration of drugs causing diabetes insipidus may decrease the pressor response. (7.5)

8 USE IN SPECIFIC POPULATIONS

- Pregnancy: May induce tonic uterine contractions. (8.1)
- Pediatric Use: Safety and effectiveness have not been established. (8.4)
- Geriatric Use: No safety issues have been identified in older patients. (8.5)

FULL PRESCRIBING INFORMATION

1 INDICATIONS AND USAGE

Vasopressin injection is indicated to increase blood pressure in adults with vasodilatory shock who remain hypotensive despite fluids and catecholamines.

2 DOSAGE AND ADMINISTRATION

2.1 Preparation of Diluted Solutions

Inspect parenteral drug products for particulate matter and discoloration prior to use, whenever solution and container permit.

Vasopressin Injection Solution for Dilution, 20 units/mL and 200 units/10 mL (20 units/mL).

Dilute vasopressin injection in 0.9% Sodium Chloride Injection or 5% Dextrose Injection prior to use for intravenous infusion. (See Table 1). Discard unused diluted solution after 18 hours at room temperature or 24 hours under refrigeration.

Table 1 Preparation of diluted solutions

Fluid restriction? | Final concentration | Mix
Fluid restriction? | Final concentration | Vasopressin Injection | Diluent
No | 0.1 units/mL | 2.5 mL (50 units) | 500 mL
Yes | 1 unit/mL | 5 mL (100 units) | 100 mL

2.2 Administration

In general, titrate to the lowest dose compatible with a clinically acceptable response.

The recommended starting dose is:

Post-cardiotomy shock: 0.03 units/minute

Septic Shock: 0.01 units/minute

Titrate up by 0.005 units/minute at 10- to 15-minute intervals until the target blood pressure is reached. There are limited data for doses above 0.1 units/minute for post-cardiotomy shock and 0.07 units/minute for septic shock. Adverse reactions are expected to increase with higher doses.

After target blood pressure has been maintained for 8 hours without the use of catecholamines, taper vasopressin injection by 0.005 units/minute every hour as tolerated to maintain target blood pressure.

3 DOSAGE FORMS AND STRENGTHS

Vasopressin injection, USP is a clear, practically colorless solution for intravenous administration available as 20 units/mL in a single-dose vial and 200 units/10 mL (20 units/mL) in a multiple-dose vial.

4 CONTRAINDICATIONS

Vasopressin injection 1 mL single-dose vial and 10 mL multiple-dose vial are contraindicated in patients with known allergy or hypersensitivity to 8-L-arginine vasopressin or chlorobutanol.

5 WARNINGS AND PRECAUTIONS

5.1 Worsening Cardiac Function

A decrease in cardiac index may be observed with use of vasopressin.

5.2 Reversible Diabetes Insipidus

Patients may experience reversible diabetes insipidus, manifested by the development of polyuria, a dilute urine, and hypernatremia, after cessation of treatment with vasopressin. Monitor serum electrolytes, fluid status, and urine output after vasopressin discontinuation. Some patients may require readministration of vasopressin or administration of desmopressin to correct fluid and electrolyte shifts.

6 ADVERSE REACTIONS

The following adverse reactions associated with the use of vasopressin were identified in the literature. Because these reactions are reported voluntarily from a population of uncertain size, it is not possible to estimate their frequency reliably or to establish a causal relationship to drug exposure.

Bleeding/lymphatic system disorders: Hemorrhagic shock, decreased platelets, intractable bleeding

Cardiac disorders: Right heart failure, atrial fibrillation, bradycardia, myocardial ischemia

Gastrointestinal disorders: Mesenteric ischemia

Hepatobiliary: Increased bilirubin levels

Renal/urinary disorders: Acute renal insufficiency

Vascular disorders: Distal limb ischemia

Metabolic: Hyponatremia

Skin: Ischemic lesions

Postmarketing Experience

Reversible diabetes insipidus [see Warnings and Precautions (5.2)].

7 DRUG INTERACTIONS

7.1 Catecholamines

Use with catecholamines is expected to result in an additive effect on mean arterial blood pressure and other hemodynamic parameters. Hemodynamic monitoring is recommended; adjust the dose of vasopressin as needed.

7.2 Indomethacin

Use with indomethacin may prolong the effect of vasopressin injection on cardiac index and systemic vascular resistance. Hemodynamic monitoring is recommended; adjust the dose of vasopressin as needed [see Clinical Pharmacology (12.3)].

7.3 Ganglionic Blocking Agents

Use with ganglionic blocking agents may increase the effect of vasopressin injection on mean arterial blood pressure. Hemodynamic monitoring is recommended; adjust the dose of vasopressin as needed [see Clinical Pharmacology (12.3)].

7.4 Drugs Suspected of Causing SIADH (Syndrome of Inappropriate Antidiuretic Hormone Secretion)

Use with drugs suspected of causing SIADH (e.g., SSRIs, tricyclic antidepressants, haloperidol, chlorpropamide, enalapril, methyldopa, pentamidine, vincristine, cyclophosphamide, ifosfamide, felbamate) may increase the pressor effect in addition to the antidiuretic effect of vasopressin injection. Hemodynamic monitoring is recommended; adjust the dose of vasopressin as needed.

7.5 Drugs Suspected of Causing Diabetes Insipidus

Use with drugs suspected of causing diabetes insipidus (e.g., demeclocycline, lithium, foscarnet, clozapine) may decrease the pressor effect in addition to the antidiuretic effect of vasopressin injection. Hemodynamic monitoring is recommended; adjust the dose of vasopressin as needed.

8 USE IN SPECIFIC POPULATIONS

8.1 Pregnancy

Risk Summary

There are no available data on vasopressin injection use in pregnant women to inform a drug associated risk of major birth defects, miscarriage, or adverse maternal or fetal outcomes. Animal reproduction studies have not been conducted with vasopressin.

Clinical Considerations

Dose Adjustments during Pregnancy and the Postpartum Period

Because of increased clearance of vasopressin in the second and third trimester, the dose of vasopressin injection may need to be increased [see Dosage and Administration (2.2) and Clinical Pharmacology (12.3)].

Maternal adverse reactions

Vasopressin injection may produce tonic uterine contractions. Vasopressin receptors are present in human uterine muscles and might not be distinguishable from oxytocin receptors.

8.2 Lactation

Risk Summary

There are no data on the presence of vasopressin injection in either human or animal milk, the effects on the breastfed infant, or the effects on milk production.

8.4 Pediatric Use

Safety and effectiveness of vasopressin injection in pediatric patients with vasodilatory shock have not been established.

8.5 Geriatric Use

Clinical studies of vasopressin did not include sufficient numbers of subjects aged 65 and over to determine whether they respond differently from younger subjects. Other reported clinical experience has not identified differences in responses between the elderly and younger patients. In general, dose selection for an elderly patient should be cautious, usually starting at the low end of the dosing range, reflecting the greater frequency of decreased hepatic, renal, or cardiac function, and of concomitant disease or other drug therapy [see Warnings and Precautions (5.1, 5.2), Adverse Reactions (6), and Clinical Pharmacology (12.3)].

10 OVERDOSAGE

Overdosage with vasopressin injection can be expected to manifest as consequences of vasoconstriction of various vascular beds (peripheral, mesenteric, and coronary) and as hyponatremia. In addition, overdosage may lead less commonly to ventricular tachyarrhythmias (including Torsade de Pointes), rhabdomyolysis, and non-specific gastrointestinal symptoms.

Direct effects will resolve within minutes of withdrawal of treatment.

11 DESCRIPTION

Vasopressin is a polypeptide hormone. Vasopressin injection is a sterile, aqueous solution of synthetic arginine vasopressin for administration. The 1 mL and 10 mL solution contains vasopressin 20 units/mL, chlorobutanol 5 mg, sodium chloride 9 mg, water for injection, and glacial acetic acid to adjust pH to 3.5.

The chemical name of vasopressin is Cyclo (1-6) L-Cysteinyl-L-Tyrosyl-L-Phenylalanyl-L- Glutaminyl-L-Asparaginyl-L-Cysteinyl-L-Prolyl-L-Arginyl-L-Glycinamide. It is a white to off-white amorphous powder, freely soluble in water. The structural formula is:

Molecular Formula: C46H65N15O12S2 Molecular Weight: 1084.23

12 CLINICAL PHARMACOLOGY

12.1 Mechanism of Action

Vasopressin causes vasoconstriction by binding to V1 receptors on vascular smooth muscle coupled to the Gq/11-phospholipase C-phosphatidyl-inositol-triphosphate pathway, resulting in the release of intracellular calcium. In addition, vasopressin stimulates antidiuresis via stimulation of V2 receptors which are coupled to adenyl cyclase.

12.2 Pharmacodynamics

At therapeutic doses exogenous vasopressin elicits a vasoconstrictive effect in most vascular beds including the splanchnic, renal and cutaneous circulation. In addition, vasopressin at pressor doses triggers contractions of smooth muscles in the gastrointestinal tract mediated by muscular V1-receptors and release of prolactin, ACTH and catecholamines via V3 receptors. At lower concentrations typical for the antidiuretic hormone vasopressin inhibits water diuresis via renal V2 receptors. In addition, vasopressin has been demonstrated to cause vasodilation in numerous vascular beds that is mediated by V2, V3, oxytocin and purinergic P2 receptors.

In patients with vasodilatory shock, vasopressin in therapeutic doses increases systemic vascular resistance and mean arterial blood pressure and reduces the dose requirements for norepinephrine. Vasopressin tends to decrease heart rate and cardiac output. The pressor effect is proportional to the infusion rate of exogenous vasopressin. The pressor effect reaches its peak within 15 minutes. After stopping the infusion, the pressor effect fades within 20 minutes. There is no evidence for tachyphylaxis or tolerance to the pressor effect of vasopressin in patients.

12.3 Pharmacokinetics

Vasopressin plasma concentrations increase linearly with increasing infusion rates from 10 microunits/kg/min to 200 microunits/kg/min. Steady state plasma concentrations are achieved after 30 minutes of continuous intravenous infusion.

Distribution

Vasopressin does not appear to bind plasma protein. The volume of distribution is 140 mL/kg.

Elimination

At infusion rates used in vasodilatory shock (0.01 units/minute to 0.1 units/minute), the clearance of vasopressin is 9 to 25 mL/min/kg in patients with vasodilatory shock. The apparent t1/2 of vasopressin at these levels is ≤10 minutes.

Metabolism

Serine protease, carboxipeptidase and disulfide oxido-reductase cleave vasopressin at sites relevant for the pharmacological activity of the hormone. Thus, the generated metabolites are not expected to retain important pharmacological activity.

Excretion

Vasopressin is predominantly metabolized and only about 6% of the dose is excreted unchanged into urine.

Specific Populations

Pregnancy: Because of a spillover into blood of placental vasopressinase, the clearance of exogenous and endogenous vasopressin increases gradually over the course of a pregnancy. During the first trimester of pregnancy, the clearance is only slightly increased. However, by the third trimester the clearance of vasopressin is increased about 4-fold and at term up to 5-fold. After delivery, the clearance of vasopressin returns to pre-conception baseline within two weeks.

Drug Interactions

Indomethacin more than doubles the time to offset for vasopressin’s effect on peripheral vascular resistance and cardiac output in healthy subjects [see Drug Interactions (7.2)].

The ganglionic blocking agent tetra-ethylammonium increases the pressor effect of vasopressin by 20% in healthy subjects [see Drug Interactions (7.3)].

Halothane, morphine, fentanyl, alfentanyl and sufentanyl do not impact exposure to endogenous vasopressin.

13 NONCLINICAL TOXICOLOGY

13.1 Carcinogenesis, Mutagenesis, Impairment of Fertility

No formal carcinogenicity or fertility studies with vasopressin have been conducted in animals. Vasopressin was found to be negative in the in vitro bacterial mutagenicity (Ames) test and the in vitro Chinese hamster ovary (CHO) cell chromosome aberration test. In mice, vasopressin has been reported to have an effect on sperm function, including motility, fertilization and embryonic development.

13.2 Animal Toxicology and/or Pharmacology

No toxicology studies were conducted with vasopressin.

14 CLINICAL STUDIES

Increases in systolic and mean blood pressure following administration of vasopressin were observed in 7 studies in septic shock and 8 studies in post-cardiotomy vasodilatory shock.

16 HOW SUPPLIED/STORAGE AND HANDLING

Vasopressin injection, USP is a clear, practically colorless solution for intravenous administration available as:

NDC 72572-860-25: A carton of 25 single-dose vials each containing vasopressin 20 units/mL.

1 mL Vial: Storage is permitted for up to 12 months at controlled room temperature (USP) 20°C to 25°C (68°F to 77°F) within the expiry date. Once removed from refrigeration, mark the unopened vial with the revised 12-month expiration date. Do not return Vasopressin to the refrigerator after it has been stored at room temperature. Discard the product after 12 months at room temperature or at the expiry date, whichever is earlier.

Store refrigerated between 2°C and 8°C (36°F and 46°F). Do not freeze.

The storage conditions and expiration periods (for the 1 mL vial) are summarized in Table 2.

Table 2

 | Unopened; Refrigerated; 2°C to 8°C (36°F to 46°F) | Unopened; Room Temperature; 20°C to 25°C (68°F to 77°F); Do not store above 25°C (77°F) | Opened; (After First Puncture)
1 mL Vial | Until manufacturer expiration date | 12 months or until manufacturer expiration date, whichever is earlier | N/A

Manufactured for:
Civica, Inc.
Lehi, Utah 84043
Manufactured by:
American Regent, Inc.
New Albany, OH 43054
RQ1141-A

PRINCIPAL DISPLAY PANEL – Container Label (1 mL)

NDC 72572-860-01
Rx Only

Vasopressin Injection, USP

20 Units per mL

For Intravenous Infusion
Must be diluted prior to use
1 mL Single-Dose Vial -
Discard Unused Portion

PRINCIPAL DISPLAY PANEL – Carton Labeling (1 mL)

NDC 72572-860-25
Rx Only
Vasopressin Injection, USP

20 Units per mL

For Intravenous Infusion
Must be diluted prior to use

25 x 1 mL Single Dose Vials
Discard Unused Portion